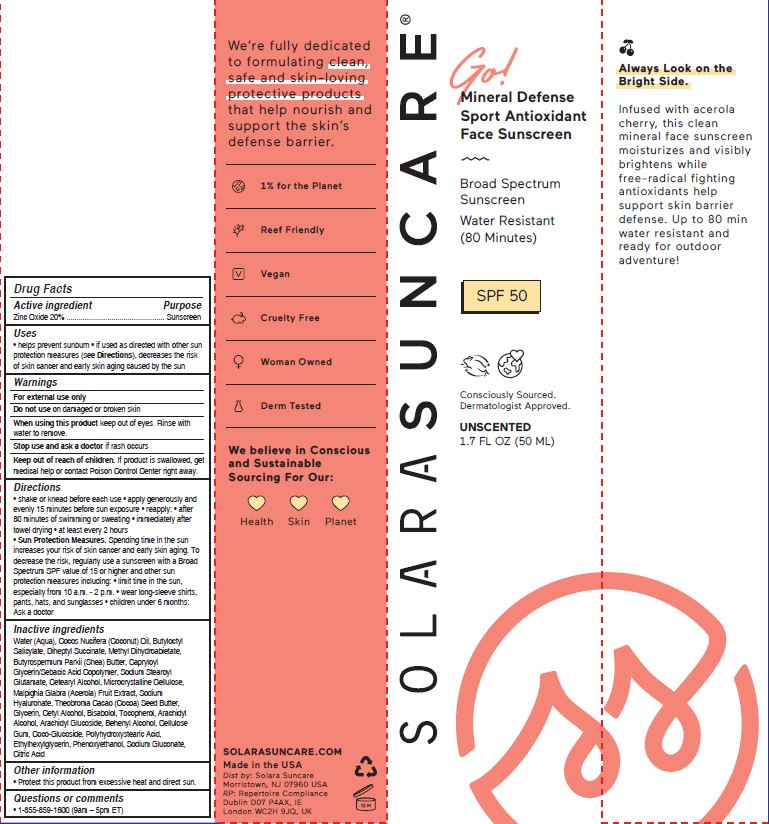 DRUG LABEL: SOLARA SUNCARE - GO VACATION GLOW

NDC: 73054-127 | Form: LOTION
Manufacturer: SOLARA SUNCARE, INC.
Category: otc | Type: HUMAN OTC DRUG LABEL
Date: 20251231

ACTIVE INGREDIENTS: ZINC OXIDE 18.9 g/100 mL
INACTIVE INGREDIENTS: WATER; COCONUT OIL; BUTYLOCTYL SALICYLATE; DIHEPTYL SUCCINATE; METHYL DIHYDROABIETATE; BUTYROSPERMUM PARKII (SHEA) BUTTER UNSAPONIFIABLES; CAPRYLOYL GLYCERIN/SEBACIC ACID COPOLYMER (2000 MPA.S); SODIUM STEAROYL GLUTAMATE; CETOSTEARYL ALCOHOL; MICROCRYSTALLINE CELLULOSE; MALPIGHIA GLABRA FRUIT; HYALURONATE SODIUM; COCOA BUTTER; GLYCERIN; CETYL ALCOHOL; LEVOMENOL; TOCOPHEROL; ARACHIDYL ALCOHOL; ARACHIDYL GLUCOSIDE; DOCOSANOL; CARBOXYMETHYLCELLULOSE SODIUM, UNSPECIFIED; COCO GLUCOSIDE; POLYHYDROXYSTEARIC ACID (2300 MW); ETHYLHEXYLGLYCERIN; PHENOXYETHANOL; SODIUM GLUCONATE; CITRIC ACID MONOHYDRATE

SOLARA (as PLD) - GO! VACATION GLOW SPF 30 (73054-127)

ACTIVE INGREDIENT

Zinc Oxide 20%

PURPOSE

Sunscreen

USES

- helps prevent sunburn
- if used as directed with other sun protection measures (see Directions), decreases the risk of skin cancer and early skin aging caused by the sun

Warnings

For external use only

Do not use on damaged or broken skin

When using this product keep out of eyes. Rinse with water to remove.

Stop use and ask a doctor if rash occurs

Keep out of reach of children. If product is swallowed, get medical help or contact Poison Control Center right away.

DIRECTIONS

- shake or knead before each use
- apply generously and evenly 15 minutes before sun exposure
- reapply:
- after 40 minutes of swimming or sweating
- immediately after towel drying
- at least every 2 hours

- Sun Protection Measures. Spending time in the sun increases your risk of skin cancer and early skin aging. To decrease the risk, regularly use asunscreen with a Broad Spectrum SPF value of 15 or higher and other sun protection measures including:
- limit time in the sun, especially from 10 a.m. - 2 p.m.
- wear long-sleeve shirts, pants, hats, and sunglasses
- children under 6 months: Ask a doctor

INACTIVE INGREDIENTS

Water (Aqua), Cocos Nucifera (Coconut) Oil, Butyloctyl Salicylate, Diheptyl Succinate, Methyl Dihydroabietate, Butyrospermum Parkii (Shea) Butter, Capryloyl Glycerin/Sebacic Acid Copolymer, Sodium Stearoyl Glutamate, Cetearyl Alcohol, Microcrystalline Cellulose, Malpighia Glabra (Acerola) Fruit Extract, Sodium Hyaluronate, Theobroma Cacao (Cocoa) Seed Butter, Glycerin, Cetyl Alcohol, Bisabolol, Tocopherol, Arachidyl Alcohol, Arachidyl Glucoside, Behenyl Alcohol, Cellulose Gum, Coco-Glucoside, Polyhydroxystearic Acid, Ethylhexylglycerin, Phenoxyethanol, Sodium Gluconate, Citric Acid

OTHER INFORMATION

- Protect this product from excessive heat and direct sun.

QUESTIONS OR COMMENTS

- 1-855-859-1600 (9am – 5pm ET)